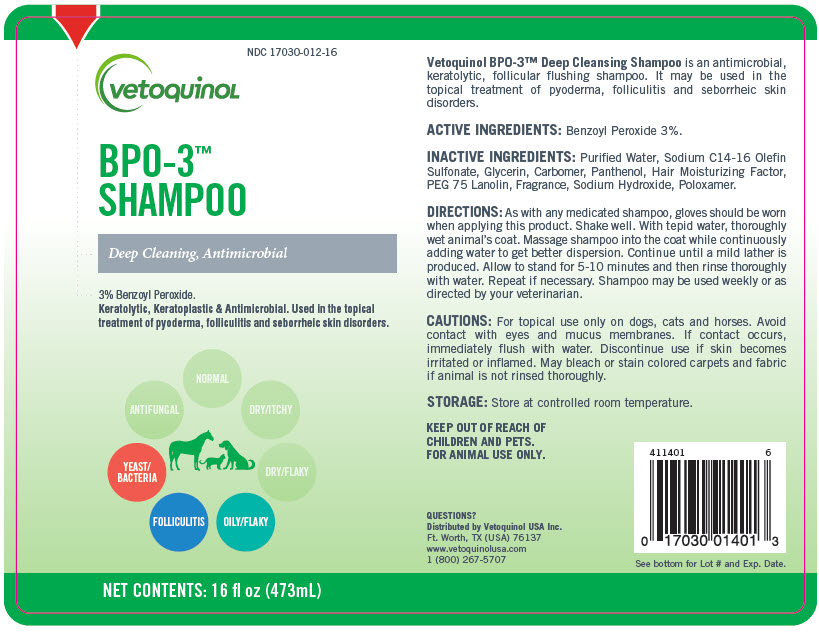 DRUG LABEL: BPO-3
NDC: 17030-012 | Form: SHAMPOO
Manufacturer: Vetoquinol USA, Inc.
Category: animal | Type: OTC ANIMAL DRUG LABEL
Date: 20221208

ACTIVE INGREDIENTS: Benzoyl Peroxide 25 mg/1 mL
INACTIVE INGREDIENTS: WATER; SODIUM C14-16 OLEFIN SULFONATE; GLYCERIN; CARBOMER HOMOPOLYMER TYPE C (ALLYL PENTAERYTHRITOL CROSSLINKED); PANTHENOL; PEG-75 LANOLIN; SODIUM HYDROXIDE; POLOXAMER 188

BPO-3™ SHAMPOO
Deep Cleaning, Antimicrobial

VETERINARY INDICATIONS

Vetoquinol BPO-3™ Deep Cleansing Shampoo is an antimicrobial, keratolytic, follicular flushing shampoo. It may be used in the topical treatment of pyoderma, folliculitis and seborrheic skin disorders.

ACTIVE INGREDIENTS: Benzoyl Peroxide 3%.

INACTIVE INGREDIENT

INACTIVE INGREDIENTS: Purified Water, Sodium C14-16 Olefin Sulfonate, Glycerin, Carbomer, Panthenol, Hair Moisturizing Factor, PEG 75 Lanolin, Fragrance, Sodium Hydroxide, Poloxamer.

DOSAGE AND ADMINISTRATION

DIRECTIONS: As with any medicated shampoo, gloves should be worn when applying this product. Shake well. With tepid water, thoroughly wet animal's coat. Massage shampoo into the coat while continuously adding water to get better dispersion. Continue until a mild lather is produced. Allow to stand for 5-10 minutes and then rinse thoroughly with water. Repeat if necessary. Shampoo may be used weekly or as directed by your veterinarian.

PRECAUTIONS

CAUTIONS: For topical use only on dogs, cats and horses. Avoid contact with eyes and mucus membranes. If contact occurs, immediately flush with water. Discontinue use if skin becomes irritated or inflamed. May bleach or stain colored carpets and fabric if animal is not rinsed thoroughly.

STORAGE: Store at controlled room temperature.

KEEP OUT OF REACH OF CHILDREN AND PETS.
FOR ANIMAL USE ONLY.

QUESTIONS?

Distributed by Vetoquinol USA Inc.
Ft. Worth, TX (USA) 76137
www.vetoquinolusa.com
1 (800) 267-5707

411401
6

See bottom for Lot # and Exp. Date.

PRINCIPAL DISPLAY PANEL - 473 mL Bottle Label

NDC 17030-012-16

vetoquinoL

BPO-3™
SHAMPOO

Deep Cleaning, Antimicrobial

3% Benzoyl Peroxide.
Keratolytic, Keratoplastic & Antimicrobial. Used in the topical
treatment of pyoderma, folliculitis and seborrheic skin disorders.

YEAST/
BACTERIA
FOLLICULITIS
OILY/FLAKY

NET CONTENTS: 16 fl oz (473mL)